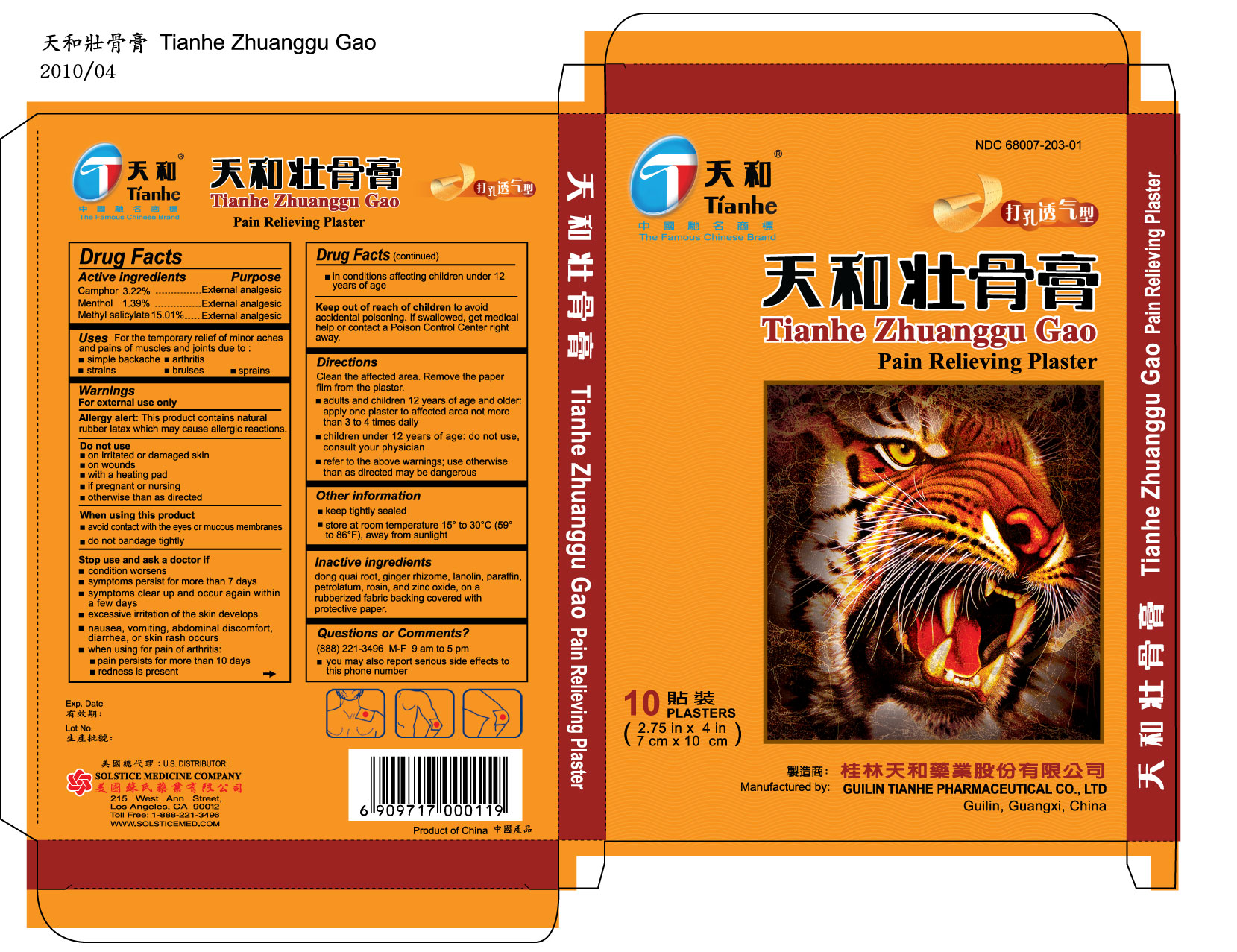 DRUG LABEL: TIANHE ZHUANGGU GAO
NDC: 68007-203 | Form: PLASTER
Manufacturer: GUILIN TIANHE PHARMACEUTICAL CO LTD
Category: otc | Type: HUMAN OTC DRUG LABEL
Date: 20100525

ACTIVE INGREDIENTS: CAMPHOR (NATURAL) 3.22 g/1 1; MENTHOL 1.39 g/1 1; METHYL SALICYLATE 15.01 g/1 1

DRUG FACTS

Active ingredients
Camphor 3.22%
Menthol 1.39%
Methyl salicylate 15.01%

Purpose

External analgesic

Uses For the temporary relief of minor aches and pains of muscles and joints due to:

- simple backache
- arthritis
- strains
- bruises
- sprains

Do not use

- on irritated or damaged skin
- on wounds
- with a heating pad
- if pregnant or nursing
- otherwise than as directed

When using this product

- avoid contact with the eyes or mucous membranes
- do not bandage tightly

Stop use and ask a doctor if

- condition worsens
- symptoms persist for more than 7 days
- symptoms clear up and occur again within a few days
- excessive irritation of the skin develops
- nausea, vomiting, abdominal discomfort, diarrhea, or skin rash occurs
- when using for pain of arthritis:
-
  - pain persists for more than 10 days
  - redness is present
  - in conditions affecting children under 12 years of age

Keep out of reach of children to avoid accidental poisoning. If swallowed, get
medical help or contact a Poison Control Center right away.

DOSAGE AND ADMINISTRATION

Directions Clean the affected area. Remove the paper film from the plaster.

- adults and children 12 years of age and older: apply one plaster to affected area not more than 3 to 4 times daily
- children under 12 years of age: do not use, consult your physician
- refer to the above warnings; use otherwise than as directed may be dangerous

Other information

- keep tightly sealed
- store at room temperature 15º to 30º C (59º to 86º F), away from sunlight

INACTIVE INGREDIENT

Inactive ingredients dong quai root, ginger rhizome, lanolin, paraffin,
petrolatum, rosin, and zinc oxide, on a rubberized fabric
backing covered with protective paper.

Questions or comments? (888) 221-3496 M-F 9 am to 5 pm

- you may also report serious side effects to this phone number

PACKAGE LABEL

TIANHE ZHANGGU GAO PAIN RELIEVING PLASTER NDC 68007-203-01 10 PLASTERS EACH PLASTER 2.27 IN X 4 IN (7 CM X 10 CM)